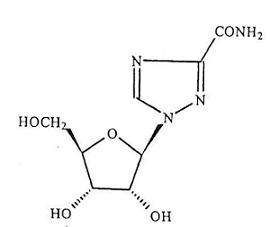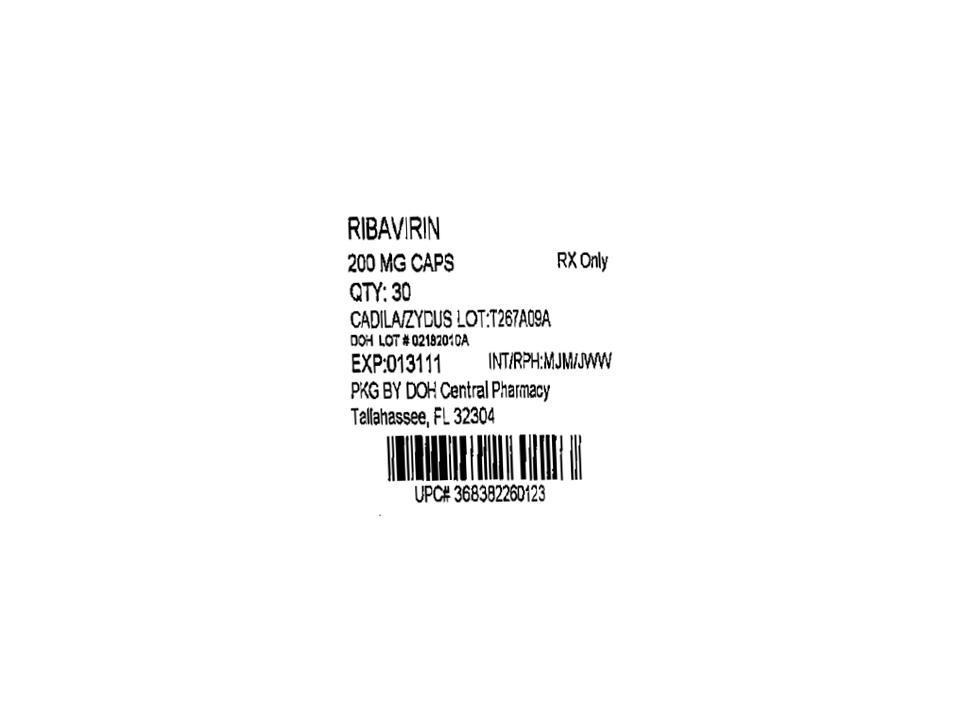 DRUG LABEL: Ribavirin
NDC: 53808-0782 | Form: TABLET, FILM COATED
Manufacturer: State of Florida DOH Central Pharmacy
Category: prescription | Type: HUMAN PRESCRIPTION DRUG LABEL
Date: 20100729

ACTIVE INGREDIENTS: RIBAVIRIN 200 mg/1 1
INACTIVE INGREDIENTS: CROSPOVIDONE; HYPROMELLOSE; FERRIC OXIDE RED ; FERRIC OXIDE YELLOW; MAGNESIUM STEARATE; CELLULOSE, MICROCRYSTALLINE; POLYETHYLENE GLYCOL; POVIDONE; SILICON DIOXIDE; TALC; TITANIUM DIOXIDE

RIBAVIRIN TABLETS

BOXED WARNING

Ribavirin tablets monotherapy is not effective for the treatment of chronic hepatitis C virus infection and should not be used alone for this indication (see WARNINGS).

The primary clinical toxicity of ribavirin is hemolytic anemia. The anemia associated with ribavirin therapy may result in worsening of cardiac disease that has led to fatal and nonfatal myocardial infarctions. Patients with a history of significant or unstable cardiac disease should not be treated with ribavirin (see WARNINGS, ADVERSE REACTIONS, and DOSAGE AND ADMINISTRATION).

Significant teratogenic and/or embryocidal effects have been demonstrated in all animal species exposed to ribavirin. In addition, ribavirin has a multiple dose half-life of 12 days, and it may persist in non-plasma compartments for as long as 6 months. Ribavirin therapy is contraindicated in women who are pregnant and in the male partners of women who are pregnant. Extreme care must be taken to avoid pregnancy during therapy and for 6 months after completion of therapy in both female patients and in female partners of male patients who are taking ribavirin therapy. At least two reliable forms of effective contraception must be utilized during treatment and during the 6-month posttreatment follow-up period (see CONTRAINDICATIONS, WARNINGS, and PRECAUTIONS: Information for Patients, and Pregnancy: Category X).

DESCRIPTION

Ribavirin tablet is a nucleoside analogue with antiviral activity. The chemical name of ribavirin is 1-ß-D-ribofuranosyl-1H-1,2,4-triazole-3-carboxamide and has the following structural formula:

The molecular formula of ribavirin is C8H12N4O5 and the molecular weight is 244.2. Ribavirin is a white crystalline powder. It is freely soluble in water and slightly soluble in anhydrous alcohol.

Each film-coated ribavirin tablet intended for oral administration contains 200 mg or 400 mg or 500 mg or 600 mg of ribavirin. In addition, each tablet contains the following inactive ingredients: crospovidone, hypromellose, iron oxide red, iron oxide yellow, magnesium stearate, microcrystalline cellulose, polyethylene glycol, povidone, silicon dioxide, talc and titanium dioxide.

Mechanism of Action

Ribavirin is a synthetic nucleoside analogue. The mechanism by which the combination of ribavirin and an interferon product exerts its effects against the hepatitis C virus has not been fully established.

CLINICAL PHARMACOLOGY

Pharmacokinetics

Multiple dose ribavirin pharmacokinetic data are available for HCV patients who received ribavirin in combination with peginterferon alfa-2a. Following administration of 1200 mg/day with food for 12 weeks mean±SD (n=39; body weight >75 kg) AUC0-12hr was 25,361±7110 ng.hr/mL and Cmax was 2748±818 ng/mL. The average time to reach Cmax was 2 hours. Trough ribavirin plasma concentrations following 12 weeks of dosing with food were 1662±545 ng/mL in HCV infected patients who received 800 mg/day (n=89), and 2112±810 ng/mL in patients who received 1200 mg/day (n=75; body weight >75 kg).

The terminal half-life of ribavirin following administration of a single oral dose of ribavirin tablet is about 120 to 170 hours. The total apparent clearance following administration of a single oral dose of ribavirin tablet is about 26 L/h. There is extensive accumulation of ribavirin after multiple dosing (twice daily) such that the Cmax at steady state was four-fold higher than that of a single dose.

Effect of Food on Absorption of Ribavirin

Bioavailability of a single oral dose of ribavirin was increased by co-administration with a high-fat meal. The absorption was slowed (Tmax was doubled) and the AUC0-192h and Cmax increased by 42% and 66%, respectively, when ribavirin tablet was taken with a high-fat meal compared with fasting conditions (see PRECAUTIONS and DOSAGE AND ADMINISTRATION).

Elimination and Metabolism

The contribution of renal and hepatic pathways to ribavirin elimination after administration of ribavirin tablet is not known. In vitro studies indicate that ribavirin is not a substrate of CYP450 enzymes.

Special Populations

Race

A pharmacokinetic study in 42 subjects demonstrated there is no clinically significant difference in ribavirin pharmacokinetics among Black (n=14), Hispanic (n=13) and Caucasian (n=15) subjects.

Renal Dysfunction

The pharmacokinetics of ribavirin following administration of ribavirin tablets have not been studied in patients with renal impairment and there are limited data from clinical trials on administration of ribavirin tablets in patients with creatinine clearance <50 mL/min. Therefore, patients with creatinine clearance <50 mL/min should not be treated with ribavirin tablets (see WARNINGS and DOSAGE AND ADMINISTRATION).

Hepatic Impairment

The effect of hepatic impairment on the pharmacokinetics of ribavirin following administration of ribavirin tablet has not been evaluated. The clinical trials of ribavirin tablets were restricted to patients with Child-Pugh class A disease.

Pediatric Patients

Pharmacokinetic evaluations in pediatric patients have not been performed.

Elderly Patients

Pharmacokinetic evaluations in elderly patients have not been performed.

Gender

Ribavirin pharmacokinetics, when corrected for weight, are similar in male and female patients.

Drug Interactions

In vitro studies indicate that ribavirin does not inhibit CYP450 enzymes.

Nucleoside Analogues

In vitro data indicate ribavirin reduces phosphorylation of lamivudine, stavudine, and zidovudine. However, no pharmacokinetic (e.g., plasma concentrations or intracellular triphosphorylated active metabolite concentrations) or pharmacodynamic (e.g., loss of HIV/HCV virologic suppression) interaction was observed when ribavirin and lamivudine (n=18), stavudine (n=10), or zidovudine (n=6) were co-administered as part of a multi-drug regimen to HCV/HIV coinfected patients) see PRECAUTIONS: Drug Interactions).

In vitro, didanosine or its active metabolite (dideoxyadenosine 5’-triphosphate) is increased when didanosine is co-administered with ribavirin, which could cause or worsen clinical toxicities (see PRECAUTIONS: Drug Interactions).

Drugs Metabolized by Cytochrome P450

There was no effect on the pharmacokinetics of representative drugs metabolized by CYP 2C9, CYP 2C19, CYP 2D6 or CYP 3A4.

Treatment with peginterferon alfa-2a once weekly for 4 weeks in healthy subjects was associated with an inhibition of P450 1A2 and a 25% increase in theophylline AUC (see PRECAUTIONS: Drug Interactions).

CLINICAL STUDIES

HCV Patients

The safety and effectiveness of peginterferon alfa-2a in combination with ribavirin tablets for the treatment of hepatitis C virus infection were assessed in two randomized controlled clinical trials. All patients were adults, had compensated liver disease, detectable hepatitis C virus, liver biopsy diagnosis of chronic hepatitis, and were previously untreated with interferon. Approximately 20% of patients in both studies had compensated cirrhosis (Child-Pugh class A). Patients coinfected with HIV were excluded from these studies.

In study NV15801 (described as study 4 in the peginterferon alfa-2a package insert), patients were randomized to receive either peginterferon alfa-2a 180 mcg sc once weekly (qw) with an oral placebo, peginterferon alfa-2a 180 mcg qw with ribavirin tablets 1000 mg po (body weight <75 kg) or 1200 mg po (body weight ≥75 kg) or interferon alfa-2b 3 MIU sc tiw plus ribavirin 1000 mg or 1200 mg po. All patients received 48 weeks of therapy followed by 24 weeks of treatment-free follow-up. Ribavirin tablets or placebo treatment assignment was blinded. Sustained virological response was defined as undetectable (<50 IU/mL) HCV RNA on or after study week 68. Peginterferon alfa-2a in combination with ribavirin tablets resulted in a higher SVR compared to peginterferon alfa-2a alone or interferon alfa-2b and ribavirin (Table 1). In all treatment arms, patients with viral genotype 1, regardless of viral load, had a lower response rate to peginterferon alfa-2a in combination with ribavirin tablets compared to patients with other viral genotypes.

Table 1 Sustained Virologic Response (SVR) to Combination Therapy (Study NV15801 [Described as study 4 in the peginterferon alfa-2a package insert.])
 | Interferon alfa-2b + Ribavirin 1000 mg or 1200 mg | Peginterferon alfa-2a + placebo | Peginterferon alfa-2a + Ribavirin Tablets 1000 mg or 1200 mg
All patients | 197/444 (44%) | 65/224 (29%) | 241/453 (53%)
Genotype 1 | 103/285 (36%) | 29/145 (20%) | 132/298 (44%)
Genotypes 2-6 | 94/159 (59%) | 36/79 (46%) | 109/155 (70%)
Difference in overall treatment response (peginterferon alfa-2a/ribavirin tablets - Interferon alfa-2b/ribavirin) was 9% (95% CI 2.3, 15.3).

In study NV15942 (described as study 5 in the peginterferon alfa-2a package insert), all patients received peginterferon alfa-2a 180 mcg sc qw and were randomized to treatment for either 24 or 48 weeks and to a ribavirin tablet dose of either 800 mg or 1000 mg/1200 mg (for body weight <75 kg/≥75 kg). Assignment to the four treatment arms was stratified by viral genotype and baseline HCV viral titer. Patients with genotype 1 and high viral titer (defined as >2 x 10^6 HCV RNA copies/mL serum) were preferentially assigned to treatment for 48 weeks.

HCV Genotypes

HCV 1 and 4 - Irrespective of baseline viral titer, treatment for 48 weeks with peginterferon alfa-2a and 1000 mg or 1200 mg of ribavirin tablets resulted in higher SVR (defined as undetectable HCV RNA at the end of the 24-week treatment-free follow-up period) compared to shorter treatment (24 weeks) and/or 800 mg ribavirin tablets.

HCV 2 and 3 - Irrespective of baseline viral titer, treatment for 24 weeks with peginterferon alfa-2a and 800 mg of ribavirin tablets resulted in a similar SVR compared to longer treatment (48 weeks) and/or 1000 mg or 1200 mg of ribavirin tablets (see Table 2).

The numbers of patients with genotype 5 and 6 were too few to allow for meaningful assessment.

Table 2 Sustained Virologic Response as a Function of Genotype (Study NV15942 [Described as study 5 in the peginterferon alfa-2a package insert.])
 | 24 Weeks Treatment |  | 48 Weeks Treatment
 | Peginterferon alfa-2a + Ribavirin Tablets 800 mg (N=207) | Peginterferon alfa-2a + Ribavirin Tablets 1000 mg or 1200 mg [1000 mg for body weight <75 kg; 1200 mg for body weight ≥75 kg.] (N=280) | Peginterferon alfa-2a + Ribavirin Tablets 800 mg (N=361) | Peginterferon alfa-2a + Ribavirin Tablets 1000 mg or 1200 mg(N=436)
Genotype 1 | 29/101 (29%) | 48/118 (41%) | 99/250 (40%) | 138/271 (51%)
Genotypes 2, 3 | 79/96 (82%) | 116/144(81%) | 75/99(76%) | 117/153 (76%)
Genotype 4 | 0/5 (0%) | 7/12 (58%) | 5/8 (63%) | 9/11 (82%)

Other Treatment Response Predictors

Treatment response rates are lower in patients with poor prognostic factors receiving pegylated interferon alpha therapy. In studies NV15801 and NV15942, treatment response rates were lower in patients older than 40 years (50% vs. 66%), in patients with cirrhosis (47% vs. 59%), in patients weighing over 85 kg (49% vs. 60%), and in patients with genotype 1 with high vs. low viral load (43% vs. 56%). African-American patients had lower response rates compared to Caucasians.

Paired liver biopsies were performed on approximately 20% of patients in studies NV15801 and NV15942. Modest reductions in inflammation compared to baseline were seen in all treatment groups.

In studies NV15801 and NV15942, lack of early virologic response by 12 weeks (defined as HCV RNA undetectable or >2log10 lower than baseline) was grounds for discontinuation of treatment. Of patients who lacked an early viral response by 12 weeks and completed a recommended course of therapy despite a protocol-defined option to discontinue therapy, 5/39 (13%) achieved an SVR. Of patients who lacked an early viral response by 24 weeks, 19 completed a full course of therapy and none achieved an SVR.

CHC and Coinfection with HIV (CHC/HIV): Study NR15961

In Study NR15961 (described as Study 6 in the peginterferon alfa-2a package insert), patients with CHC/HIV were randomized to receive either peginterferon alfa-2a 180 mcg sc once weekly (qw) plus an oral placebo, peginterferon alfa-2a 180 mcg qw plus ribavirin tablets 800 mg po daily or interferon alfa-2a, 3 MIU sc tiw plus ribavirin tablets 800 mg po daily. All patients received 48 weeks of therapy and sustained virologic response (SVR) was assessed at 24 weeks of treatment-free follow-up. Ribavirin tablets or placebo treatment assignment was blinded in the peginterferon alfa-2a treatment arms. All patients were adults, had compensated liver disease, detectable hepatitis C virus, liver biopsy diagnosis of chronic hepatitis C, and were previously untreated with interferon. Patients also had CD4+ cell count (200 cells/µL or CD4+ cell count (100 cells/µL but <200 cells/µL and HIV-1 RNA <5000 copies/mL, and stable status of HIV. Approximately 15% of patients in the study had cirrhosis. Results are shown in Table 3.

Table 3 Sustained Virologic Response in Patients With Chronic Hepatitis C Coinfected With HIV (Study NR15961 [Peginterferon alfa-2a + Ribavirin vs. Peginterferon alfa-2a; Peginterferon alfa-2a + Ribavirin vs. Interferon alfa-2a + Ribavirin p-value <0.0001 (Cochran-Mantel-Haenszel).])
 | Interferon-a + Ribavirin Tablets 800 mg | Peginterferon alfa-2a + Placebo | Peginterferon alfa-2a + Ribavirin Tablets 800 mg
 | (N=289) | (N=289) | (N=290)
All patients | 33 (11%) | 58 (20%) | 116 (40%)
Genotype 1 | 12/171 (7%) | 24/175 (14%) | 51/176 (29%)
Genotypes 2, 3 | 18/89 (20%) | 32/90 (36%) | 59/95 (62%)

Treatment response rates are lower in CHC/HIV patients with poor prognostic factors (including HCV genotype 1, HCV RNA >800,000 IU/mL, and cirrhosis) receiving pegylated interferon alpha therapy. Geographic region is not a prognostic factor for response. However, poor prognostic factors occur more frequently in the US population than in the non-US population.

Of the patients who did not demonstrate either undetectable HCV RNA or at least a 2log10 reduction from baseline in HCV RNA titer by 12 weeks of peginterferon alfa-2a and ribavirin tablets combination therapy, 2% (2/85) achieved an SVR.

In CHC patients with HIV coinfection who received 48 weeks of peginterferon alfa-2a alone or in combination with ribavirin tablets treatment, mean and median HIV RNA titers did not increase above baseline during treatment or 24 weeks posttreatment.

INDICATIONS AND USAGE

Ribavirin tablets in combination with peginterferon alfa-2a are indicated for the treatment of adults with chronic hepatitis C virus infection who have compensated liver disease and have not been previously treated with interferon alpha. Patients in whom efficacy was demonstrated included patients with compensated liver disease and histological evidence of cirrhosis (Child-Pugh class A) and patients with HIV disease that is clinically stable (e.g., antiretroviral therapy not required or receiving stable antiretroviral therapy).

CONTRAINDICATIONS

Ribavirin tablet is contraindicated in:

- Patients with known hypersensitivity to ribavirin tablets or to any component of the tablet.
- Women who are pregnant.
- Men whose female partners are pregnant.
- Patients with hemoglobinopathies (e.g., thalassemia major or sickle-cell anemia).

Ribavirin tablets and peginterferon alfa-2a combination therapy is contraindicated in patients with:

- Autoimmune hepatitis.
- Hepatic decompensation (Child-Pugh score greater than 6; class B and C) in cirrhotic CHC monoinfected patients before or during treatment.
- Hepatic decompensation with Child-Pugh score greater than or equal to 6 in cirrhotic CHC patients coinfected with HIV before or during treatment.

WARNINGS

Ribavirin tablets must not be used alone because ribavirin monotherapy is not effective for the treatment of chronic hepatitis C virus infection. The safety and efficacy of ribavirin tablets have only been established when used together with peginterferon alfa-2a (pegylated interferon alfa-2a, recombinant).

Ribavirin tablets and peginterferon alfa-2a should be discontinued in patients who develop evidence of hepatic decompensation during treatment.

There are significant adverse events caused by ribavirin tablets/peginterferon alfa-2a therapy, including severe depression and suicidal ideation, hemolytic anemia, suppression of bone marrow function, autoimmune and infectious disorders, pulmonary dysfunction, pancreatitis, and diabetes. The peginterferon alfa-2a package insert and MEDICATION GUIDE should be reviewed in their entirety prior to initiation of combination treatment for additional safety information.

General

Treatment with ribavirin tablets and peginterferon alfa-2a should be administered under the guidance of a qualified physician and may lead to moderate to severe adverse experiences requiring dose reduction, temporary dose cessation or discontinuation of therapy.

Pregnancy

Ribavirin may cause birth defects and/or death of the exposed fetus. Extreme care must be taken to avoid pregnancy in female patients and in female partners of male patients. Ribavirin has demonstrated significant teratogenic and/or embryocidal effects in all animal species in which adequate studies have been conducted. These effects occurred at doses as low as one twentieth of the recommended human dose of ribavirin. RIBAVIRIN TABLETS THERAPY SHOULD NOT BE STARTED UNLESS A REPORT OF A NEGATIVE PREGNANCY TEST HAS BEEN OBTAINED IMMEDIATELY PRIOR TO PLANNED INITIATION OF THERAPY. Patients should be instructed to use at least two forms of effective contraception during treatment and for six-months after treatment has been stopped. Pregnancy testing should occur monthly during ribavirin tablets therapy and for 6 months after therapy has stopped (see CONTRAINDICATIONS and PRECAUTIONS : Information for Patients and Pregnancy: Category X).

Anemia

The primary toxicity of ribavirin is hemolytic anemia (hemoglobin <10 g/dL), which was observed in approximately 13% of all ribavirin tablets and peginterferon alfa-2a treated patients in clinical trials (see PRECAUTIONS: Laboratory Tests). The anemia associated with ribavirin tablets occurs within 1 to 2 weeks of initiation of therapy. BECAUSE THE INITIAL DROP IN HEMOGLOBIN MAY BE SIGNIFICANT, IT IS ADVISED THAT HEMOGLOBIN OR HEMATOCRIT BE OBTAINED PRETREATMENT AND AT WEEK 2 AND WEEK 4 OF THERAPY OR MORE FREQUENTLY IF CLINICALLY INDICATED. Patients should then be followed as clinically appropriate.

Fatal and nonfatal myocardial infarctions have been reported in patients with anemia caused by ribavirin. Patients should be assessed for underlying cardiac disease before initiation of ribavirin therapy. Patients with pre-existing cardiac disease should have electrocardiograms administered before treatment, and should be appropriately monitored during therapy. If there is any deterioration of cardiovascular status, therapy should be suspended or discontinued (see DOSAGE AND ADMINISTRATION: Ribavirin Tablets Dosage Modification Guidelines). Because cardiac disease may be worsened by drug induced anemia, patients with a history of significant or unstable cardiac disease should not use ribavirin tablets (see ADVERSE REACTIONS).

Hepatic Failure

Chronic hepatitis C (CHC) patients with cirrhosis may be at risk of hepatic decompensation and death when treated with alpha interferons, including peginterferon alfa-2a. Cirrhotic CHC patients coinfected with HIV receiving highly active antiretroviral therapy (HAART) and interferon alfa-2a with or without ribavirin appear to be at increased risk for the development of hepatic decompensation compared to patients not receiving HAART. In Study NR15961 (described as Study 6 in the peginterferon alfa-2a package insert), among 129 CHC/HIV cirrhotic patients receiving HAART, 14 (11%) of these patients across all treatment arms developed hepatic decompensation resulting in 6 deaths. All 14 patients were on NRTIs, including stavudine, didanosine, abacavir, zidovudine, and lamivudine. These small numbers of patients do not permit discrimination between specific NRTIs or the associated risk. During treatment, patients’ clinical status and hepatic function should be closely monitored, and peginterferon alfa-2a treatment should be immediately discontinued if decompensation (Child-Pugh score ≥6) is observed (see CONTRAINDICATIONS).

Hypersensitivity:

Severe acute hypersensitivity reactions (e.g., urticaria, angioedema, bronchoconstriction, and anaphylaxis) have been rarely observed during alpha interferon and ribavirin therapy. If such reaction occurs, therapy with peginterferon alfa-2a and ribavirin should be discontinued and appropriate medical therapy immediately instituted. Serious skin reactions including vesiculobullous eruptions, reactions in the spectrum of Stevens Johnson Syndrome (erythema multiforme major) with varying degrees of skin and mucosal involvement and exfoliative dermatitis (erythroderma) have been rarely reported in patients receiving peginterferon alfa-2a with and without ribavirin. Patients developing signs or symptoms of severe skin reactions must discontinue therapy.(see ADVERSE REACTIONS: Postmarketing Experience).

Pulmonary

Pulmonary symptoms, including dyspnea, pulmonary infiltrates, pneumonitis and occasional cases of fatal pneumonia, have been reported during therapy with ribavirin and interferon. In addition, sarcoidosis or the exacerbation of sarcoidosis has been reported. If there is evidence of pulmonary infiltrates or pulmonary function impairment, the patient should be closely monitored, and if appropriate, combination ribavirin tablets/peginterferon alfa-2a treatment should be discontinued.

Other

Ribavirin tablets and peginterferon alfa-2a therapy should be suspended in patients with signs and symptoms of pancreatitis, and discontinued in patients with confirmed pancreatitis.

Ribavirin tablets should not be used in patients with creatinine clearance <50 mL/min (see CLINICAL PHARMACOLOGY: Special Populations).

Ribavirin tablets must be discontinued immediately and appropriate medical therapy instituted if an acute hypersensitivity reaction (e.g., urticaria, angioedema, bronchoconstriction, anaphylaxis) develops. Transient rashes do not necessitate interruption of treatment.

PRECAUTIONS

The safety and efficacy of ribavirin tablets and peginterferon alfa-2a therapy for the treatment of adenovirus, RSV, parainfluenza or influenza infections have not been established. Ribavirin tablets should not be used for these indications. Ribavirin for inhalation has a separate package insert, which should be consulted if ribavirin inhalation therapy is being considered.

The safety and efficacy of ribavirin tablets and peginterferon alfa-2a therapy have not been established in liver or other organ transplant patients, patients with decompensated liver disease due to hepatitis C virus infection, patients who are non-responders to interferon therapy or patients coinfected with HBV or HIV and a CD4+ cell count <100 cells/μL.

Information for Patients

Patients must be informed that ribavirin may cause birth defects and/or death of the exposed fetus. Ribavirin tablets therapy must not be used by women who are pregnant or by men whose female partners are pregnant. Extreme care must be taken to avoid pregnancy in female patients and in female partners of male patients taking ribavirin tablets therapy and for 6 months posttherapy. Ribavirin tablets therapy should not be initiated until a report of a negative pregnancy test has been obtained immediately prior to initiation of therapy. Patients must perform a pregnancy test monthly during therapy and for 6 months posttherapy.

Female patients of childbearing potential and male patients with female partners of childbearing potential must be advised of the teratogenic/embryocidal risks and must be instructed to practice effective contraception during ribavirin tablets therapy and for 6 months posttherapy. Patients should be advised to notify the healthcare provider immediately in the event of a pregnancy (see CONTRAINDICATIONS and WARNINGS).

The most common adverse event associated with ribavirin is anemia, which may be severe (see ADVERSE REACTIONS). Patients should be advised that laboratory evaluations are required prior to starting ribavirin tablets therapy and periodically thereafter (see Laboratory Tests). It is advised that patients be well hydrated, especially during the initial stages of treatment.

Patients who develop dizziness, confusion, somnolence, and fatigue should be cautioned to avoid driving or operating machinery.

Patients should be informed regarding the potential benefits and risks attendant to the use of ribavirin tablets. Instructions on appropriate use should be given, including review of the contents of the enclosed MEDICATION GUIDE, which is not a disclosure of all or possible adverse effects.

Patients should be advised to take ribavirin tablets with food.

Laboratory Tests

Before beginning ribavirin tablets therapy, standard hematological and biochemical laboratory tests must be conducted for all patients. Pregnancy screening for women of childbearing potential must be done.

After initiation of therapy, hematological tests should be performed at 2 weeks and 4 weeks and biochemical tests should be performed at 4 weeks. Additional testing should be performed periodically during therapy. Monthly pregnancy testing should be done during combination therapy and for 6 months after discontinuing therapy.

The entrance criteria used for the clinical studies of ribavirin tablets and peginterferon alfa-2a combination therapy may be considered as a guideline to acceptable baseline values for initiation of treatment:

- Platelet count ≥ 90,000 cells/mm^3 (as low as 75,000 cells/mm^3 in patients with cirrhosis or 70,000 cells/mm^3 in patients with CHC and HIV)
- Absolute neutrophil count (ANC) ≥ 1500 cells/mm^3
- TSH and T4 within normal limits or adequately controlled thyroid function
- ECG (see WARNINGS)
- CD4+ cell count ≥ 200 cells/µL or CD4+ cell count ≥100 cells/µL but <200 cells/µL and HIV-1 RNA <5000 copies/mL in patients coinfected with HIV
- Hemoglobin ≥12 g/dL for women and ≥13 g/dL for men in CHC monoinfected patients
- Hemoglobin ≥11 g/dL for women and ≥12 g/dL for men in patients with CHC and HIV

The maximum drop in hemoglobin usually occurred during the first 8 weeks of initiation of ribavirin tablets therapy. Because of this initial acute drop in hemoglobin, it is advised that a complete blood count should be obtained pretreatment and at week 2 and week 4 of therapy or more frequently if clinically indicated. Additional testing should be performed periodically during therapy. Patients should then be followed as clinically appropriate.

Drug Interactions

Results from a pharmacokinetic sub-study demonstrated no pharmacokinetic interaction between peginterferon alfa-2a and ribavirin.

Nucleoside Analogues

NRTIs

In Study NR15961 among the CHC/HIV coinfected cirrhotic patients receiving NRTIs cases of hepatic decompensation (some fatal) were observed (see WARNINGS: Hepatic Failure).

Patients receiving peginterferon alfa-2a/ribavirin tablets and NRTIs should be closely monitored for treatment associated toxicities. Physicians should refer to prescribing information for the respective NRTIs for guidance regarding toxicity management. In addition, dose reduction or discontinuation of peginterferon alfa-2a, ribavirin tablets or both should also be considered if worsening toxicities are observed (see WARNINGS, PRECAUTIONS, and DOSAGE AND ADMINISTRATION: Dose Modifications).

Didanosine

Co-administration of ribavirin tablets and didanosine is not recommended. Reports of fatal hepatic failure, as well as peripheral neuropathy, pancreatitis, and symptomatic hyperlactatemia/lactic acidosis have been reported in clinical trials (see CLINICAL PHARMACOLOGY: Drug Interactions).

Zidovudine

In Study NR15961, patients who were administered zidovudine in combination with peginterferon alfa-2a/ribavirin tablets developed severe neutropenia (ANC <500) and severe anemia (hemoglobin <8 g/dL) more frequently than similar patients not receiving zidovudine (neutropenia 15% vs. 9%) (anemia 5% vs. 1%).

Lamivudine, Stavudine, and Zidovudine

In vitro studies have shown ribavirin can reduce the phosphorylation of pyrimidine nucleoside analogs such as lamivudine, stavudine, and zidovudine. No evidence of a pharmacokinetic or pharmacodynamic interaction was seen when ribavirin was co-administered with lamivudine, stavudine, and/or zidovudine in HIV/HCV coinfected patients (see CLINICAL PHARMACOLOGY: Drug Interactions).

Carcinogenesis

In a p53 (+/-) mouse carcinogenicity study and a rat 2-year carcinogenicity study at doses up to the maximum tolerated doses of 100 mg/kg/day and 60 mg/kg/day, respectively, ribavirin was not oncogenic. On a body surface area basis, these doses are approximately 0.5 and 0.6 times the maximum recommended human 24-hour dose of ribavirin.

Mutagenesis

Ribavirin demonstrated mutagenic activity in the in vitro mouse lymphoma assay. No clastogenic activity was observed in an in vivo mouse micronucleus assay at doses up to 2000 mg/kg. However, results from studies published in the literature show clastogenic activity in the in vivo mouse micronucleus assay at oral doses up to 2000 mg/kg. A dominant lethal assay in rats was negative, indicating that if mutations occurred in rats they were not transmitted through male gametes. However, potential carcinogenic risk to humans cannot be excluded.

Impairment of Fertility

In a fertility study in rats, ribavirin showed a marginal reduction in sperm counts at the dose of 100 mg/kg/day with no effect on fertility. Upon cessation of treatment, total recovery occurred after 1 spermatogenesis cycle. Abnormalities in sperm were observed in studies in mice designed to evaluate the time course and reversibility of ribavirin-induced testicular degeneration at doses of 15 to 150 mg/kg/day (approximately 0.1 to 0.8 times the maximum recommended human 24-hour dose of ribavirin) administered for 3 to 6 months. Upon cessation of treatment, essentially total recovery from ribavirin-induced testicular toxicity was apparent within 1 or 2 spermatogenic cycles.

Female patients of childbearing potential and male patients with female partners of childbearing potential should not receive ribavirin tablets unless the patient and his/her partner are using effective contraception (two reliable forms). Based on a multiple dose half-life (t1/2) of ribavirin of 12 days, effective contraception must be utilized for 6 months posttherapy (i.e., 15 half-lives of clearance for ribavirin).

No reproductive toxicology studies have been performed using peginterferon alfa-2a in combination with ribavirin tablets. However, peginterferon alfa-2a and ribavirin when administered separately, each has adverse effects on reproduction. It should be assumed that the effects produced by either agent alone would also be caused by the combination of the two agents.

Pregnancy

Pregnancy: Category X (see CONTRAINDICATIONS)

Ribavirin produced significant embryocidal and/or teratogenic effects in all animal species in which adequate studies have been conducted. Malformations of the skull, palate, eye, jaw, limbs, skeleton, and gastrointestinal tract were noted. The incidence and severity of teratogenic effects increased with escalation of the drug dose. Survival of fetuses and offspring was reduced.

In conventional embryotoxicity/teratogenicity studies in rats and rabbits, observed no-effect dose levels were well below those for proposed clinical use (0.3 mg/kg/day for both the rat and rabbit; approximately 0.06 times the recommended human 24-hour dose of ribavirin). No maternal toxicity or effects on offspring were observed in a peri/postnatal toxicity study in rats dosed orally at up to 1 mg/kg/day (approximately 0.01 times the maximum recommended human 24-hour dose of ribavirin).

Treatment and Posttreatment: Potential Risk to the Fetus

Ribavirin is known to accumulate in intracellular components from where it is cleared very slowly. It is not known whether ribavirin is contained in sperm, and if so, will exert a potential teratogenic effect upon fertilization of the ova. In a study in rats, it was concluded that dominant lethality was not induced by ribavirin at doses up to 200 mg/kg for 5 days (up to 1.7 times the maximum recommended human dose of ribavirin). However, because of the potential human teratogenic effects of ribavirin, male patients should be advised to take every precaution to avoid risk of pregnancy for their female partners.

Ribavirin tablets should not be used by pregnant women or by men whose female partners are pregnant. Female patients of childbearing potential and male patients with female partners of childbearing potential should not receive ribavirin tablets unless the patient and his/her partner are using effective contraception (two reliable forms) during therapy and for 6 months posttherapy.

Ribavirin Pregnancy Registry

A Ribavirin Pregnancy Registry has been established to monitor maternal-fetal outcomes of pregnancies of female patients and female partners of male patients exposed to ribavirin during treatment and for six months following cessation of treatment. Healthcare providers and patients are encouraged to report such cases by calling 1-800-593-2214.

Animal Toxicology

Long-term study in the mouse and rat (18 to 24 months; dose 20 to 75 and 10 to 40 mg/kg/day, respectively, approximately 0.1 to 0.4 times the maximum human daily dose of ribavirin) have demonstrated a relationship between chronic ribavirin exposure and an increased incidence of vascular lesions (microscopic hemorrhages) in mice. In rats, retinal degeneration occurred in controls, but the incidence was increased in ribavirin-treated rats.

Nursing Mothers

It is not known whether ribavirin is excreted in human milk. Because many drugs are excreted in human milk and to avoid any potential for serious adverse reactions in nursing infants from ribavirin, a decision should be made either to discontinue nursing or therapy with ribavirin tablets, based on the importance of the therapy to the mother.

Pediatric Use

Safety and effectiveness of ribavirin tablets have not been established in patients below the age of 18.

Geriatric Use

Clinical studies of ribavirin tablets and peginterferon alfa-2a did not include sufficient numbers of subjects aged 65 or over to determine whether they respond differently from younger subjects. Specific pharmacokinetic evaluations for ribavirin in the elderly have not been performed. The risk of toxic reactions to this drug may be greater in patients with impaired renal function. Ribavirin tablets should not be administered to patients with creatinine clearance <50 mL/min. (see CLINICAL PHARMACOLOGY: Special Populations).

Effect of Gender

No clinically significant differences in the pharmacokinetics of ribavirin were observed between male and female subjects.

ADVERSE REACTIONS

Peginterferon alfa-2a in combination with ribavirin tablets causes a broad variety of serious adverse reactions (see BOXED WARNING and WARNINGS).

The most common life-threatening or fatal events induced or aggravated by peginterferon alfa-2a and ribavirin tablets were depression, suicide, relapse of drug abuse/overdose, and bacterial infections, each occurred at a frequency of <1%. Hepatic decompensation occurred in 2% (10/574) of CHC/HIV patients (see WARNINGS: Hepatic Failure).

In all studies, one or more serious adverse reactions occurred in 10% of CHC monoinfected patients and in 19% of CHC/HIV receiving peginterferon alfa-2a alone or in combination with ribavirin tablets. The most common serious adverse event (3% in CHC and 5% in CHC/HIV) was bacterial infection (e.g., sepsis, osteomyelitis, endocarditis, pyelonephritis, pneumonia). Other SAEs occurred at a frequency of <1% and included: suicide, suicidal ideation, psychosis, aggression, anxiety, drug abuse and drug overdose, angina, hepatic dysfunction, fatty liver, cholangitis, arrhythmia, diabetes mellitus, autoimmune phenomena (e.g., hyperthyroidism, hypothyroidism, sarcoidosis, systemic lupus erythematosus, rheumatoid arthritis), peripheral neuropathy, aplastic anemia, peptic ulcer, gastrointestinal bleeding, pancreatitis, colitis, corneal ulcer, pulmonary embolism, coma, myositis, cerebral hemorrhage, thrombotic thrombocytopenic purpura, psychotic disorder, and hallucination.

Nearly all patients in clinical trials experienced one or more adverse events. The most commonly reported adverse reactions were psychiatric reactions, including depression, insomnia, irritability, anxiety, and flu-like symptoms such as fatigue, pyrexia, myalgia, headache and rigors. Other common reactions were anorexia, nausea and vomiting, diarrhea, arthralgias, injection site reactions, alopecia, and pruritus.

Ten percent of CHC monoinfected patients receiving 48 weeks of therapy with peginterferon alfa-2a in combination with ribavirin tablets discontinued therapy; 16% of CHC/HIV coinfected patients discontinued therapy. The most common reasons for discontinuation of therapy were psychiatric, flu-like syndrome (e.g., lethargy, fatigue, headache), dermatologic and gastrointestinal disorders and laboratory abnormalities (thrombocytopenia, neutropenia, and anemia).

Overall 39% of patients with CHC or CHC/HIV required modification of peginterferon alfa-2a and/or ribavirin tablets therapy. The most common reason for dose modification of peginterferon alfa-2a in CHC and CHC/HIV patients was for laboratory abnormalities; neutropenia (20% and 27%, respectively) and thrombocytopenia (4% and 6%, respectively). The most common reason for dose modification of ribavirin tablets in CHC and CHC/HIV patients was anemia (22% and 16%, respectively).

Peginterferon alfa-2a dose was reduced in 12% of patients receiving 1000 mg to 1200 mg ribavirin tablets for 48 weeks and in 7% of patients receiving 800 mg ribavirin tablets for 24 weeks. Ribavirin tablet dose was reduced in 21% of patients receiving 1000 mg to 1200 mg ribavirin tablets for 48 weeks and in 12% of patients receiving 800 mg ribavirin tablets for 24 weeks.

Chronic hepatitis C monoinfected patients treated for 24 weeks with peginterferon alfa-2a and 800 mg ribavirin tablets were observed to have lower incidence of serious adverse events (3% vs. 10%), hemoglobin <10 g/dL (3% vs. 15%), dose modification of peginterferon alfa-2a (30% vs. 36%) and ribavirin tablets (19% vs. 38%), and of withdrawal from treatment (5% vs. 15%) compared to patients treated for 48 weeks with peginterferon alfa-2a and 1000 mg or 1200 mg ribavirin tablets. On the other hand, the overall incidence of adverse events appeared to be similar in the two treatment groups.

Because clinical trials are conducted under widely varying and controlled conditions, adverse reaction rates observed in clinical trials of a drug cannot be directly compared to rates in the clinical trials of another drug. Also, the adverse event rates listed here may not predict the rates observed in a broader patient population in clinical practice.

Table 4 Adverse Reactions Occurring in ≥5% of Patients in Chronic Hepatitis C Clinical Trials (Study NV15801 [Described as study 4 in the peginterferon alfa-2a package insert.])
Body System | CHC Combination Therapy Study NV15801
 | Peginterferon alfa-2a 180 mcg + 1000 mg or 1200 mg Ribavirin Tablets 48 week | Interferon alfa-2b + 1000 mg or 1200 mg Ribavirin Capsules 48 week
 | N=451 | N=443
 | % | %
Application Site Disorders; Injection site reaction | 23 | 16
Endocrine Disorders; Hypothyroidism | 4 | 5
Flu-like Symptoms and Signs; Fatigue/Asthenia Pyrexia Rigors Pain | 65 41 25 10 | 68 55 37 9
Gastrointestinal; Nausea/vomiting Diarrhea Abdominal pain Dry mouth Dyspepsia | 25 11 8 4 6 | 29 10 9 7 5
Hematologic [Severe hematologic abnormalities(lymphocyte <0.5 x 10^9/L; hemoglobin <10 g/dL; neutrophil <0.75 x 10^9/L; platelet <50 x 10^9/L).]; Lymphopenia Anemia Neutropenia Thrombocytopenia | 14 11 27 5 | 12 11 8 <1
Metabolic and Nutritional; Anorexia Weight decrease | 24 10 | 26 10
Musculoskeletal, Connective Tissue and Bone; Myalgia Arthralgia Back pain | 40 22 5 | 49 23 5
Neurological; Headache Dizziness (excluding vertigo) Memory impairment | 43 14 6 | 49 14 5
Psychiatric; Irritability/Anxiety/Nervousness Insomnia Depression Concentration impairment Mood alteration | 33 30 20 10 5 | 38 37 28 13 6
Resistance Mechanism Disorders; Overall | 12 | 10
Respiratory, Thoracic and Mediastinal; Dyspnea Cough Dyspnea exertional | 13 10 4 | 14 7 7
Skin and Subcutaneous Tissue
Alopecia | 28 | 33
Pruritus | 19 | 18
Dermatitis | 16 | 13
Dry Skin | 10 | 13
Rash | 8 | 5
Sweating Increased | 6 | 5
Eczema | 5 | 4
Visual Disorders
Vision Blurred | 5 | 2

Common Adverse Reactions in CHC With HIV Coinfection

The adverse event profile of coinfected patients treated with peginterferon alfa-2a and ribavirin tablets in Study NR15961 was generally similar to that shown for monoinfected patients in Study NV15801 (Table 4). Events occurring more frequently in coinfected patients were neutropenia (40%), anemia (14%), thrombocytopenia (8%), weight decrease (16%), and mood alteration (9%).

Laboratory Test Values

Anemia due to hemolysis is the most significant toxicity of ribavirin therapy. Anemia (hemoglobin <10 g/dL) was observed in 13% of all ribavirin tablets and peginterferon alfa-2a combination-treated patients in clinical trials. The maximum drop in hemoglobin occurred during the first 8 weeks of initiation of ribavirin therapy (see DOSAGE AND ADMINISTRATION: Dose Modifications).

Postmarketing Experience:

The reactions have been identified and reported during post-approval use of peginterferon alfa-2a following adverse therapy: dehydration, hearing impairment, hearing loss, and serious skin reactions (see WARNINGS: Hypersensitivity).

OVERDOSAGE

No cases of overdose with ribavirin tablets have been reported in clinical trials. Hypocalcemia and hypomagnesemia have been observed in persons administered greater than the recommended dosage of ribavirin. In most of these cases, ribavirin was administered intravenously at dosages up to and in some cases exceeding four times the recommended maximum oral daily dose.

DOSAGE AND ADMINISTRATION

CHC Monoinfection

The recommended dose of ribavirin tablet is provided in Table 5. The recommended duration of treatment for patients previously untreated with ribavirin and interferon is 24 to 48 weeks.

The daily dose of ribavirin tablet is 800 mg to 1200 mg administered orally in two divided doses. The dose should be individualized to the patient depending on baseline disease characteristics (e.g., genotype), response to therapy, and tolerability of the regimen (see Table 5).

In the pivotal clinical trials, patients were instructed to take ribavirin tablets with food; therefore, patients are advised to take ribavirin tablets with food.

Table 5 Peginterferon alfa-2a and Ribavirin Tablets Dosing Recommendations
Genotype | Peginterferon alfa-2a Dose | Ribavirin Tablets Dose | Duration
Genotype 1, 4 | 180 mcg | <75 kg = 1000 mg ≥75 kg = 1200 mg | 48 weeks 48 weeks
Genotype 2, 3 | 180 mcg | 800 mg | 24 weeks
Genotypes non-1 showed no increased response to treatment beyond 24 weeks (see Table 2). Data on genotypes 5 and 6 are insufficient for dosing recommendations.

CHC with HIV Coinfection

The recommended dose for hepatitis C in HCV/HIV coinfected patients is peginterferon alfa-2a 180 mcg sc once weekly and ribavirin tablets 800 mg po daily for a total of 48 weeks, regardless of genotype.

Dose Modifications

If severe adverse reactions or laboratory abnormalities develop during combination ribavirin tablets/peginterferon alfa-2a therapy, the dose should be modified or discontinued, if appropriate, until the adverse reactions abate. If intolerance persists after dose adjustment, ribavirin tablets/peginterferon alfa-2a therapy should be discontinued.

Ribavirin tablets should be administered with caution to patients with pre-existing cardiac disease (see Table 6). Patients should be assessed before commencement of therapy and should be appropriately monitored during therapy. If there is any deterioration of cardiovascular status, therapy should be stopped (see WARNINGS).

Table 6 Ribavirin Tablets Dosage Modification Guidelines
Laboratory Values | Reduce Only Ribavirin Tablets Dose to 600 mg/day [One 200 mg tablet in the morning and two 200 mg tablets in the evening.] if: | Discontinue Ribavirin Tablets if:
Hemoglobin in patients with no cardiac disease | <10 g/dL | <8.5 g/dL
Hemoglobin in patients with history of stable cardiac disease | ≥2 g/dL decrease in hemoglobin during any 4 week period treatment | <12 g/dL despite 4 weeks at reduced dose

Once ribavirin tablet has been withheld due to either a laboratory abnormality or clinical manifestation, an attempt may be made to restart ribavirin tablets at 600 mg daily and further increase the dose to 800 mg daily depending upon the physician's judgment. However, it is not recommended that ribavirin tablets be increased to its original assigned dose (1000 mg to 1200 mg).

Renal Impairment

Ribavirin tablets should not be used in patients with creatinine clearance <50 mL/min (see WARNINGS and CLINICAL PHARMACOLOGY: Special Populations).

HOW SUPPLIED

Ribavirin Tablets, 200 mg are light pink to pink, round, biconvex, beveled, film-coated tablets debossed with the logo of ‘ZC19’ on one side, other side plain.

Ribavirin Tablets, 400 mg are light pink to pink, capsule shaped, biconvex, film-coated tablets debossed with 'ZD' and '07' on one side and plain on other side.

Ribavirin Tablets, 500 mg are light pink to pink, modified capsule shaped, biconvex, film-coated tablets debossed with 'ZC56' on one side and plain on the other side.

Ribavirin Tablets, 600 mg are light pink to pink, modified capsule shaped, biconvex, film-coated tablets debossed with 'ZD' and '08' on one side and plain on other side.

They are supplied by State of Florida DOH Central Pharmacy as follows:

NDC | Strength | Quantity/Form | Color | Source Prod. Code
53808-0782-1 | 200 mg | 30 Tablets in a Blister Pack | LIGHT PINK TO PINK | 68382-260

Storage Conditions

Store at 20° - 25°C (68° - 77°F) [see USP Controlled Room Temperature].

Keep bottle tightly closed.

MEDICATION GUIDE

Read this Medication Guide carefully before you start taking ribavirin tablets and read the Medication Guide each time you get more ribavirin tablets. There may be new information. This information does not take the place of talking to your healthcare provider about your medical condition or your treatment.

What is the most important information I should know about ribavirin tablets?

1. Ribavirin tablets may cause birth defects or death of an unborn child. Therefore, if you are pregnant or your partner is pregnant or plans to become pregnant, do not take ribavirin tablets. Female patients and female partners of male patients being treated with ribavirin tablets must not becomepregnant during treatment and for 6 months after treatment has stopped.

During this time you must have pregnancy tests that show you are not pregnant. You must also use 2 effective forms of birth control during therapy and for 6 months after stopping therapy. Male patients should use a condom with spermicide as one of the two forms.

If pregnancy occurs, report the pregnancy to your healthcare provider right away. (See " What should I avoid while taking ribavirin tablets? ")

If you or a female sexual partner becomes pregnant, you should tell your healthcare provider. There is a Ribavirin Pregnancy Registry that collects information about pregnancy outcomes of female patients and female partners of male patients exposed to ribavirin. You or your healthcare provider are encouraged to contact the Registry at 1-800-593-2214.

2. Ribavirin tablets can cause a dangerous drop in your red blood cell count.

Ribavirin tablets can cause anemia, which is a decrease in the number of red blood cells. This can be dangerous, especially if you have heart or breathing problems. This may cause a worsening of heart (cardiovascular) or circulatory problems. Some patients may get chest pain and rarely, a heart attack. Patients with a history of heart disease have the highest chance of this. Tell your healthcare provider, before taking ribavirin tablets if you have or have ever had any heart or breathing problems. Your healthcare provider should check your red blood cell count before you start treatment with ribavirin tablets and often during the first 4 weeks of treatment. Your red blood cell count may be done more often if you have any heart or breathing problems.

3. Do not take ribavirin tablets alone to treat hepatitis C virus infection.

Ribavirin tablet does not treat hepatitis C virus infections by itself. Ribavirin tablets should be used in combination with peginterferon alfa-2a to treat continuing (chronic) hepatitis C virus infections. You should read the Medication Guide for peginterferon alfa-2a because it has additional important information about treatment that is not covered in this Medication Guide. Your healthcare provider or pharmacist should give you a copy of the peginterferon alfa-2a Medication Guide.

What is ribavirin tablet?

Ribavirin tablet is the antiviral medicine containing ribavirin. It is used in combination with a medicine called peginterferon alfa-2a to treat some adults with chronic hepatitis C whose liver still works normally, and who have not been treated before with a medicine called an interferon alpha. It is not known how ribavirin tablets and peginterferon alfa-2a work together to fight hepatitis C virus infections.

It is not known if treatment with ribavirin tablets and peginterferon alfa-2a combination therapy can cure hepatitis C or if it can prevent liver damage (cirrhosis), liver failure or liver cancer that is caused by hepatitis C virus infections. It is not known if treatment with ribavirin tablets and peginterferon alfa-2a combination therapy will prevent an infected person from spreading the hepatitis C virus to another person.

Treatment with ribavirin tablet has not been studied in children under 18 years of age.

Who should not take ribavirin tablets?

Do not use ribavirin tablets if:

- You are a female and you are pregnant or plan to become pregnant during treatment or during the 6 months after your treatment has ended. (See " What is the most important information I should know about ribavirin tablets? " and " What should I avoid while taking ribavirin tablets?")
- You are a male patient with a female sexual partner who is pregnant or plans to become pregnant at any time while you are being treated with ribavirin tablets or during the 6 months after your treatment has ended. (See "What is the most important information I should know about ribavirin tablets?" and "What should I avoid while taking ribavirin tablets?")
- You are breast feeding. We do not know if ribavirin tablets can pass through your milk and if it can harm your baby. You will need to choose either to breast feed or take ribavirin tablets, but not both.
- You have a liver disease called autoimmune hepatitis (hepatitis caused by your immune system attacking your liver).
- You have unstable or severe liver disease.
- You are allergic to any of the ingredients in ribavirin tablets. The active ingredient in ribavirin tablets is ribavirin. See the end of this Medication Guide for a list of all the ingredients in ribavirin tablets.

Tell your healthcare provider before starting treatment with ribavirin tablets in combination with peginterferon alfa-2a (see also the peginterferon alfa-2a Medication Guide) if you have any of the following medical conditions:

- mental health problems, such as depression or anxiety: Ribavirin tablets and peginterferon alfa-2a combination therapy may make them worse. Tell your healthcare provider if you are being treated or had treatment in the past for any mental problems, including depression, thoughts of ending your life (suicidal thoughts) or a feeling of loss of contact with reality, such as hearing voices or seeing things that are not there (psychosis). Tell your healthcare provider if you take any medicines for these problems.
- high blood pressure, heart problems or have had a heart attack. Ribavirin tablets may worsen heart problems such as high blood pressure, increased heart rate, and chest pain. Tell your healthcare provider if you have or had a heart problem. Patients who have had certain heart problems should not take ribavirin tablets.
- blood disorders, including anemia (low red blood cell count), thalassemia (Mediterranean anemia) and sickle-cell anemia. Ribavirin tablets can reduce the number of red blood cells you have. This may make you feel dizzy or weak and could worsen any heart problems you might have.
- kidney problems. If your kidneys do not work properly, you may have worse side effects from ribavirin tablets treatment and require a lower dose.
- liver problems (other than hepatitis C virus infection).
- organ transplant, and you are taking medicine that keeps your body from rejecting your transplant (suppresses your immune system).
- thyroid disease. Ribavirin tablets and peginterferon alfa-2a combination therapy may make your thyroid disease worse or harder to treat. Ribavirin tablets and peginterferon alfa-2a treatment may be stopped if you develop thyroid problems that cannot be controlled by medicine.
- have or had drug or alcohol addiction or abuse.
- cancer.
- infection with hepatitis B virus.
- diabetes. Ribavirin tablets and peginterferon alfa-2a combination therapy may make your diabetes worse or harder to treat.
- past interferon treatment for hepatitis C virus infection that did not work for you.

Tell your healthcare provider about all the medicines you take, including prescription and non-prescription medicines, vitamins or herbal supplements. Some medicines can cause serious side effects if taken while you also take ribavirin tablets. Some medicines may affect how ribavirin tablets work or ribavirin tablets may affect how your other medicines work. Be especially sure to tell your healthcare provider if you take any medicines to treat HIV.

For more information see the peginterferon alfa-2a Medication Guide.

How should I take ribavirin tablets?

- Your healthcare provider will determine the right dose of ribavirin tablets based on your weight.
- Take ribavirin tablets 1 time in the morning and 1 time at night (2 times a day). Take ribavirin tablets the same 2 times each day.
- Take ribavirin tablets with food.
- It is very important to follow your dosing schedule and your healthcare provider's instructions on how to take your medicines.
- Take ribavirin tablets for as long as it is prescribed, and do not take more than your healthcare provider prescribes.
- If you miss a dose of ribavirin tablets and remember the same day, take the missed dose as soon as you remember. If the whole day has passed, ask your healthcare provider what to do. Do not take 2 doses at the same time.
- Your healthcare provider may adjust your dose of ribavirin tablets based on blood tests that show your response to treatment and side effects you may have.
- Females taking ribavirin tablets or female sexual partners of male patients taking ribavirin tablets must have a pregnancy test:
  - before treatment begins
  - every month during treatment
  - for 6 months after treatment ends to make sure there is no pregnancy

It is also important not to use other ribavirin medicines without talking to your healthcare provider. Please see the peginterferon alfa-2a Medication Guide for the proper use of peginterferon alfa-2a injection.

What should I avoid while taking ribavirin tablets?

Avoid the following during ribavirin tablets treatment:

- Do not get pregnant. If you or your sexual partner get pregnant during treatment with ribavirin tablets or in the 6 months after treatment ends, tell your healthcare provider right away. (See " What is the most important information I should know about ribavirin tablets? ")
  Talk with your healthcare provider about birth control methods and how to avoid pregnancy. You must use extreme care to avoid pregnancy during and for 6 months after treatment in female and male patients.
- Do not take ribavirin tablets alone to treat your hepatitis C virus infection. Ribavirin tablets should be used in combination with peginterferon alfa-2a to treat chronic hepatitis C virus infections. (See " What is the most important information I should know about ribavirin tablets? ")
- Do not breast feed. Ribavirin tablets may pass through your milk and may harm your baby.
- Do not drink alcohol, including beer, wine, and liquor. This may make your liver disease worse.
- Do not drive or operate machinery if ribavirin tablet makes you feel tired, dizzy or confused.
- Do not take other medicines unless your healthcare provider knows about them. Take only medicines prescribed or approved by your healthcare provider. These include prescription and non-prescription medicines, vitamins or herbal supplements. Talk to your healthcare provider before starting any new medicine.

What are the possible side effects of ribavirin tablets?

The most serious possible side effects of ribavirin tablets are:

- Harm to unborn children. Ribavirin tablets may cause birth defects or death of an unborn child. (For more details, see " What is the most important information I should know about ribavirin tablets? ")
- Anemia. Anemia is a reduction in the number of red blood cells you have. Anemia can be dangerous, especially if you have heart or breathing problems. Tell your healthcare provider right away if you feel tired, have chest pain or shortness of breath. These may be signs of low red blood cell counts.
- Liver Problems. Some patients may develop worsening of liver function. Some of the symptoms may include stomach bloating, confusion, brown urine, and yellow eyes. Tell your healthcare provider immediately if any of these symptoms occur.

Call your healthcare provider right away if you have any of the following symptoms. They may be signs of a serious side effect of ribavirin tablets and peginterferon alfa-2a treatment.

- trouble breathing
- hives or swelling
- chest pain
- severe stomach pain or low back pain
- bloody diarrhea or bloody stools (bowel movements). These may look like black tar.
- bruising or unusual bleeding
- change in your vision
- high fever (temperature greater than 100.5°F)
- you have psoriasis (a skin disease) and it gets worse
- you become very depressed or think about suicide (ending your life)
- Skin rash can occur in patients taking peginterferon alfa-2a. In some patients a rash can be serious. If you develop a rash with fever, blisters, or sores in your mouth, nose or eyes or conjunctivitis (red or inflamed eyes, like "pink eye"), stop using peginterferon alfa-2a and call your doctor right away.

The most common side effects of ribavirin tablets are likely to be the same as for other ribavirin products. These are:

- feeling tired
- nausea and appetite loss
- rash and itching
- cough

These are not all the possible side effects of ribavirin tablets treatment. For more information, ask your doctor or pharmacist and see the peginterferon alfa-2a Medication Guide.

Call your doctor for medical advice about side effects. You may report side effects to FDA at 1-800-FDA-1088.

What should I know about hepatitis C infection?

Hepatitis C infection is a disease caused by a virus that infects the liver. Hepatitis C is more serious for some people than others. Most people who get hepatitis C carry the virus in their blood for the rest of their lives. Most of these people will have some liver damage, but many do not feel sick from the disease. In some people, the liver becomes badly damaged and scarred. This is called cirrhosis. Cirrhosis can cause the liver to stop working. Some people may get liver cancer or liver failure from the hepatitis C virus.

Hepatitis C virus is spread from one person to another by contact with an infected person's blood. You should talk to your healthcare provider about ways to prevent you from infecting others.

How should I store ribavirin tablets?

Store between 20° - 25°C (68° - 77°F).

Please refer to the peginterferon alfa-2a Medication Guide for storage information about peginterferon alfa-2a injection.

General information about the safe and effective use of ribavirin tablets

Medicines are sometimes prescribed for purposes other than those listed in a Medication Guide. Do not use ribavirin tablets for a condition for which it was not prescribed. Do not give ribavirin tablets to other people, even if they have the same symptoms that you have.

This Medication Guide summarizes the most important information about ribavirin tablets. If you would like more information, talk with your healthcare provider. You can ask your healthcare provider or pharmacist for information about ribavirin tablets that is written for healthcare professionals.

What are the ingredients in ribavirin tablets?

Active Ingredient: ribavirin

Inactive Ingredients: crospovidone, hypromellose, iron oxide red, iron oxide yellow, magnesium stearate, microcrystalline cellulose, polyethylene glycol, povidone, silicon dioxide, talc and titanium dioxide.

This Medication Guide has been approved by the US Food and Drug Administration.

Manufactured by:

Cadila Healthcare Ltd.

Ahmedabad, India

Distributed by:

Zydus Pharmaceuticals USA Inc.

Princeton, NJ 08540

This Product was Repackaged By:

State of Florida DOH Central Pharmacy
104-2 Hamilton Park Drive
Tallahassee, FL 32304
United States